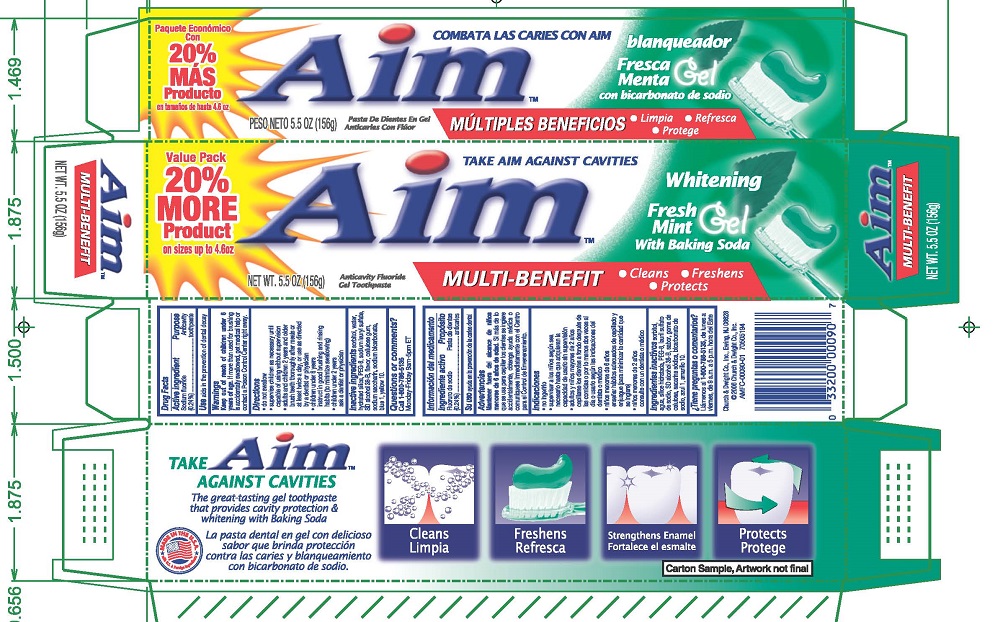 DRUG LABEL: AIM Whitening
NDC: 10237-636 | Form: GEL, DENTIFRICE
Manufacturer: Church & Dwight Co., Inc.
Category: otc | Type: HUMAN OTC DRUG LABEL
Date: 20250127

ACTIVE INGREDIENTS: SODIUM FLUORIDE 2.4 mg/1 g
INACTIVE INGREDIENTS: SORBITOL; WATER; HYDRATED SILICA; PEG-8 STEARATE; SODIUM LAURYL SULFATE; ALCOHOL; CARBOXYMETHYLCELLULOSE SODIUM, UNSPECIFIED; SODIUM BICARBONATE; SACCHARIN SODIUM; FD&C BLUE NO. 1; D&C YELLOW NO. 10

AIM Whitening Fresh Mint Gel with Baking Soda

Active ingredients
Sodium fluoride (0.24%)

Purpose
Anticavity toothpaste

INDICATIONS AND USAGE

Use aids in the prevention of dental decay

Warnings
Keep out of reach of children under 6 years of age .

WARNINGS

If more than used for brushing is accidentally swallowed, get medical help or contact a Poison Control Center right away.

DOSAGE AND ADMINISTRATION

Directions do not swallow supervise children as necessary until capable of using without supervision

adults and children 2 years and olderbrush teeth thoroughly after meals or at least twice a day, or use as directed by a dentist or physician
children under 6 yearsinstruct in good brushing and rinsing habits (to minimize swallowing)
children under 2 yearsask a dentist or physician

INACTIVE INGREDIENT

Inactive ingredientssorbitol, water, hydrated silica, PEG-8, sodium lauryl sulfate, SD alcohol 38-B, flavor, sodium bicarbonate, cellulose gum, sodium saccharin, blue 1, yellow 10.

Questions or comments? Call 1-800-786-5135Monday-Friday 9am-5pm ET

Principal Display Panel

TAKE AIM AGAINST CAVITIES

AIM

Whitening With Baking Soda

Fresh Mint

Gel

NET WT. 6 OZ. (170g)

Anticavity Fluoride Gel Toothpaste

MULTI-BENEFIT

Cleans Freshens Protects